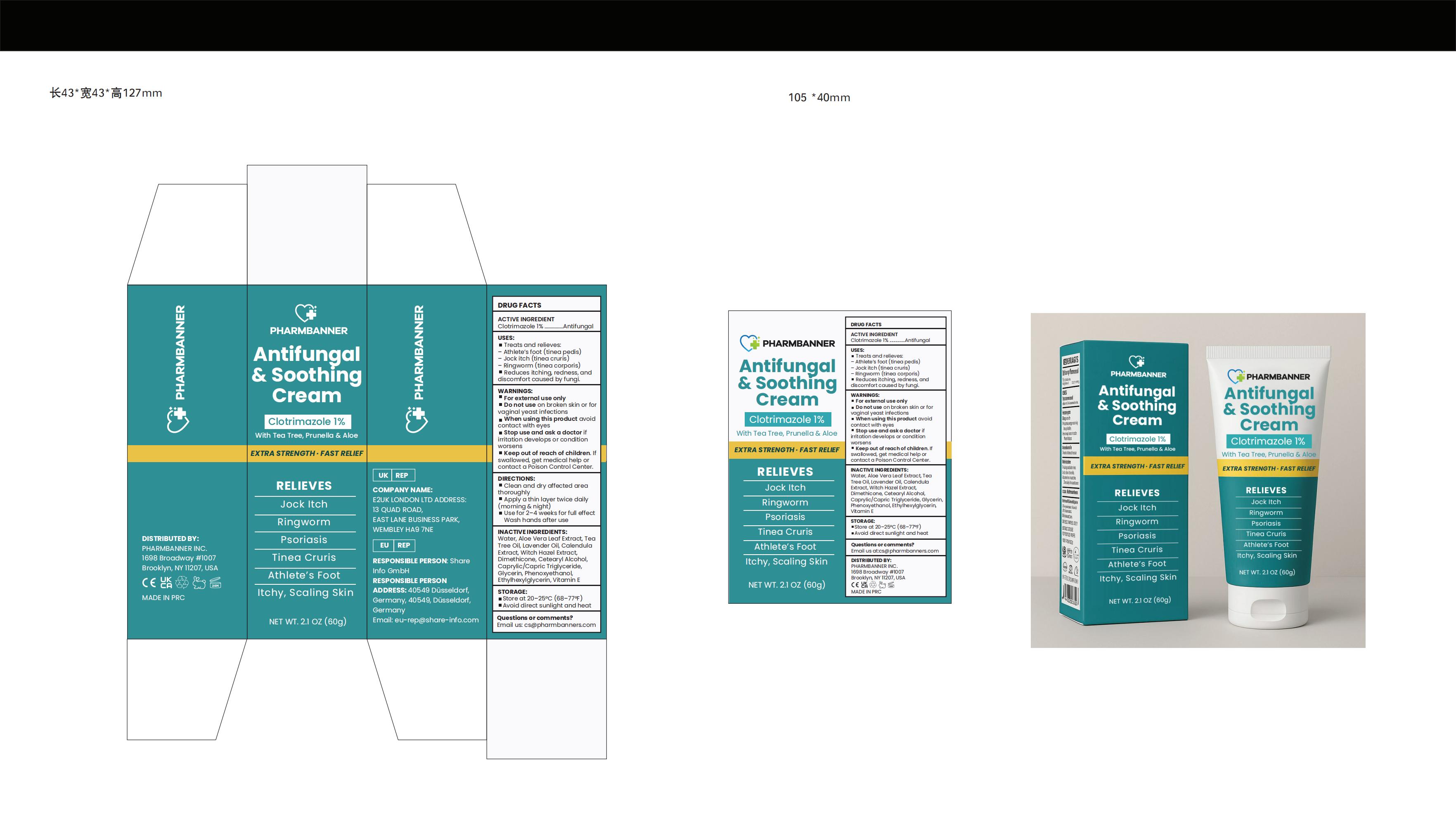 DRUG LABEL: PHARMBANNER Antifungal Soothing Cream
NDC: 83818-017 | Form: CREAM
Manufacturer: Shenzhen Xinxin Yunhai Technology Co., Ltd.
Category: otc | Type: HUMAN OTC DRUG LABEL
Date: 20260212

ACTIVE INGREDIENTS: CLOTRIMAZOLE 1 g/100 g
INACTIVE INGREDIENTS: LAVENDER OIL; CALENDULA ARVENSIS WHOLE; GLYCERIN; WITCH HAZEL; ALOE VERA LEAF; WATER; TEA TREE OIL; DIMETHICONE; CETEARYL ALCOHOL; CAPRYLIC/CAPRIC TRIGLYCERIDE; PHENOXYETHANOL; ETHYLHEXYLGLYCERIN; VITAMIN E POLYETHYLENE GLYCOL SUCCINATE

83818-017 Update Manufacturer

Active Ingredient

Clotrimazole 1%

Purpose

Antifungal

Use

■ Treats and relieves:
- Athlete's foot (tinea pedis) - Jock itch (tinea cruris) - Ringworm (tinea corporis)
■ Reduces itching, redness, and discomfort caused by fungi.

Warnings

For external use only

Do not use

on broken skin or for vaginal yeast infections

When Using

avoid contact with eyes

Stop Use

if irritation develops or condition worsens

Ask Doctor

if irritation develops or condition worsens

Keep Out Of Reach Of Children

If swallowed, get medical help or contact a Poison Control Center.

Directions

■ Clean and dry affected area thoroughly
■ Apply a thin layer twice daily (morning & night)
■ Use for 2-4 weeks for full effect. Wash hands after use

Other information

■ Store at 20-25°C (68-77°F)
■ Avoid direct sunlight and heat

Inactive ingredients

Water, Aloe Vera Leaf Extract, Tea Tree Oil, Lavender Oil, Calendula Extract, Witch Hazel Extract, Dimethicone, Cetearyl Alcohol, Caprylic/Capric Triglyceride, Glycerin, Phenoxyethanol, Ethylhexylglycerin, Vitamin E

Questions

Email us: cs@pharmbanners.com